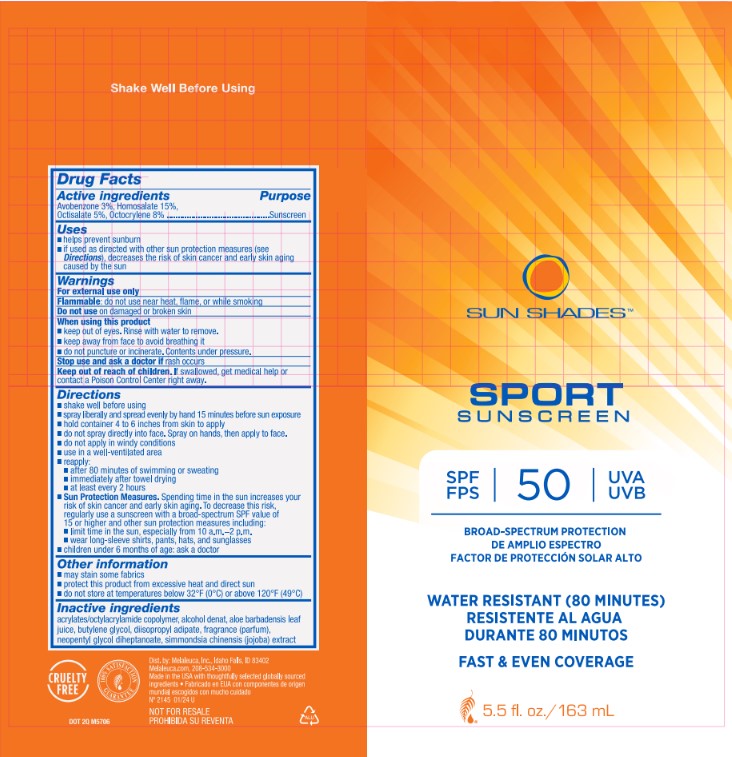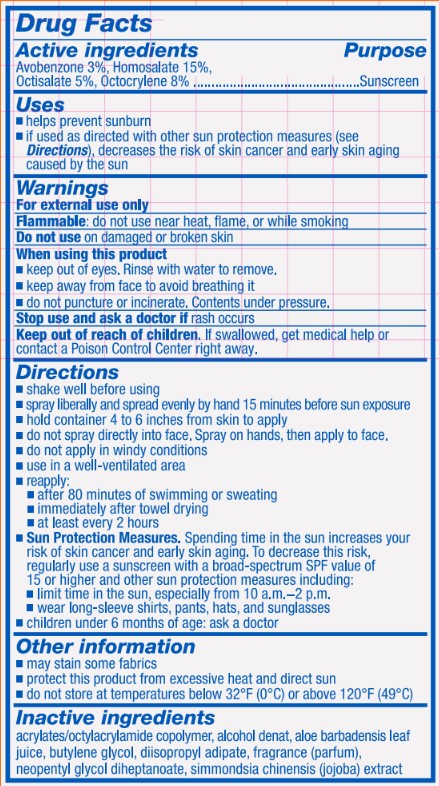 DRUG LABEL: Sun Shades Sunscreen
NDC: 54473-404 | Form: SPRAY
Manufacturer: Melaleuca Inc.
Category: otc | Type: HUMAN OTC DRUG LABEL
Date: 20251222

ACTIVE INGREDIENTS: OCTOCRYLENE 13.04 g/163 mL; OCTISALATE 8.15 g/163 mL; AVOBENZONE 4.89 g/163 mL; HOMOSALATE 24.45 g/163 mL
INACTIVE INGREDIENTS: NEOPENTYL GLYCOL DIHEPTANOATE; DIISOPROPYL ADIPATE; ALOE VERA LEAF; ACRYLATE/ISOBUTYL METHACRYLATE/N-TERT-OCTYLACRYLAMIDE COPOLYMER (40000 MW); SIMMONDSIA CHINENSIS LEAF; PARFUMIDINE; ALCOHOL; BUTYLENE GLYCOL

Sun Shades Sport Spray 50

Active Ingredients

Avobenzone 3%, Homosalate 15%, Octisalate 5%, Octocrylene 8%

Purpose

Sunscreen

Uses

- helps prevent sunburn
- if used as directed with other sun protection measures (see Directions), decreases the risk of skin cancer and early skin aging caused by the sun

Warnings

For external use only
Flammable: do not use near heat, flame, or while smoking

Do not use on damaged or broken skin

Do not use on damaged or broken skin

When using this product

- keep out of eyes. Rinse with water to remove.
- keep away from face to avoid breathing it
- do not puncture or incinerate. Contents under pressure.

Stop use and ask a doctor if rash occurs

Keep out of reach of children. If swallowed, get medical help or contact a Poison Control Center right away.

Directions

- shake well before using
- spray liberally and spread evenly by hand 15 minutes before sun exposure
- hold container 4 to 6 inches from skin to apply
- do not spray directly into face. Spray on hands, then apply to face.
- do not apply in windy conditions
- use a well-ventilated area
- reapply
  - after 80 minutes of swimming or sweating
  - immediately after towel drying
  - at least every 2 hours
  - Sun Protection Measures. spending time in the sun increases your risk of skin cancer and early skin aging. To decrease this risk, regularly use a sunscreen with a broad-spectrum SPF value of 15 or higher and other sun protection measures including:
  - limit time in the sun, especially from 10 a.m.-2 p.m.
  - wear long-sleeve shirts, pants, hats, and sunglasses
  - children under 6 months of age: ask a doctor

Other information

- may stain some fabrics
- protect this product from excessive heat and direct sun
- do not store at temperatures below 32 F (0 C) or above 120 F (49 C)

INACTIVE INGREDIENT

acrylates/octylacrylamide copolymer, alcohol denat, aloe barbadensis leaf juice, butylene glycol, diisopropyl adipate, fragrance (parfum), neopentyl glycol diheptanoate, simmondsia chinensis (jojoba) extract